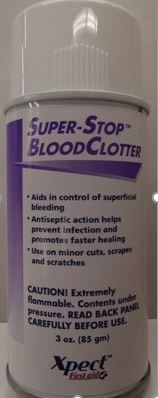 DRUG LABEL: Super-Stop BloodClotter
NDC: 42961-223 | Form: AEROSOL, SPRAY
Manufacturer: Cintas Corp
Category: otc | Type: HUMAN OTC DRUG LABEL
Date: 20250926

ACTIVE INGREDIENTS: BENZETHONIUM CHLORIDE 0.2 mg/100 mg; LIDOCAINE 4 mg/100 mg
INACTIVE INGREDIENTS: ISOBUTANE; ISOPROPYL MYRISTATE; KARAYA GUM; BUTANE; PROPANE; SILICON DIOXIDE; 3-(TRIETHOXYSILYL)PROPYLAMINE; SORBITAN MONOOLEATE; TALC; TRAGACANTH

Xpect Super Stop BloodClotter

Active ingredients

Benzethonium Chloride 0.2% w/w

Lidocaine 4% w/w

Purpose

Topical Antiseptic

Topical Anesthetic

Uses

- for help in control of superficial bleeding
- for temporary relief of pain and to help protect against infection in
- minor cuts
- minor scrapes
- minor burns

Warnings

For external use only

Flammable

- keep away from fire or flame

Do not use

- in or near eyes or other mucus membranes
- on large portion of the body
- in case of deep or puncture wounds
- on raw surfaces
- on blistered areas
- on animal bites
- on serious burns

When using this product

- avoid spraying in eyes
- contents under pressure
- do not puncture or incinerate
- do not store at temperatures above 120°F
- use only as directed
- intentional misuse by deliberately concentrating and inhaling the contents can be harmful or fatal

Stop use and ask a doctor if

- redness, swelling, or irritation occurs
- infection occurs
- condition worsens or symptoms persist for more than 7 days

Keep out of reach of children. If swallowed, get medical help or contact a Poison Control Center right away.

Directions

- shake can well before using
- hold 6-8 inches from moist injured area
- spray until area is covered
- scab-like cover will gradually disappear as healing takes place or may be removed with soap and water
- for adult institutional use only
- not intended for use on children

Inactive Ingredients

Isobutane, Isopropyl Myristate, Karaya, N-Butane, Propane, Silica, Sorbitan Monooleate, Talc, and Tragacanth

NDC Package Code 42961-210-01

Super-Stop™ BloodClotter

- Aids in control of superficial bleeding
- Antiseptic action helps prevent infection and promotes faster healing
- Use on minor cuts, scrapes and scratches

CAUTION! Extremely flammable. Contents under pressure. READ BACK PANEL CAREFULLY BEFORE USE.

3 oz. (85 gm)

Xpect™ First aid